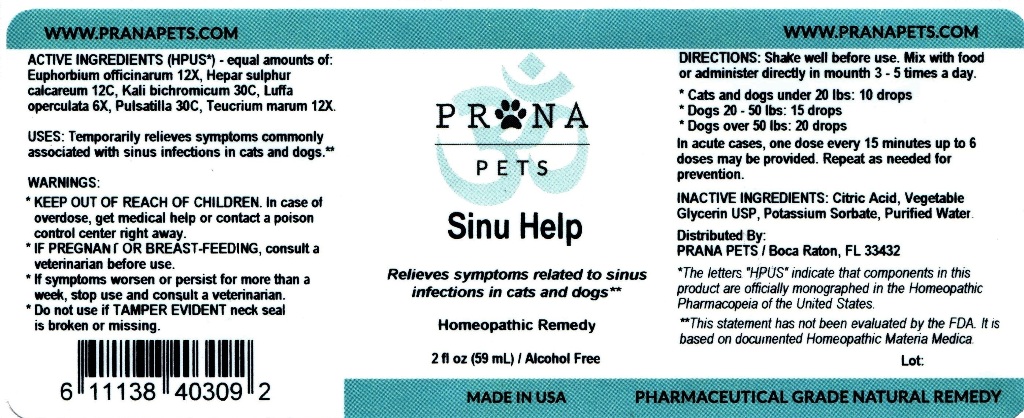 DRUG LABEL: Sinu Help
NDC: 86066-002 | Form: LIQUID
Manufacturer: Surefreight Global LLC, DBA PRANAPETS
Category: homeopathic | Type: OTC ANIMAL DRUG LABEL
Date: 20171128

ACTIVE INGREDIENTS: EUPHORBIA RESINIFERA RESIN 12 [hp_X]/59 mL; CALCIUM SULFIDE 12 [hp_C]/59 mL; POTASSIUM DICHROMATE 30 [hp_C]/59 mL; LUFFA OPERCULATA FRUIT 6 [hp_X]/59 mL; PULSATILLA VULGARIS 30 [hp_C]/59 mL; TEUCRIUM MARUM 12 [hp_X]/59 mL
INACTIVE INGREDIENTS: WATER; GLYCERIN; CITRIC ACID MONOHYDRATE; POTASSIUM SORBATE

Sinu Help

ACTIVE INGREDIENT

ACTIVE INGREDIENTS (HPUS*) - equal amounts of: Euphorbium officinarum 12X, Hepar sulphur calcareum 12C, Kali bichromicum 30C, Luffa operculata 6X, Pulsatilla 30C, Teucrium marum 12X.

* The letters "HPUS" indicate that components in this product are officially monographed in the Homeopathic Pharmacopeia of the United States.

INDICATIONS AND USAGE

USES: Temporarily relieves symptoms commonly associated with sinus infections in cats and dogs.**

** This statement has not been evaluated by the FDA. It is based on documented Homeopathic Materia Medica.

WARNINGS:

- KEEP OUT OF REACH OF CHILDREN. In case of overdose, get medical help or contact a poison control center right away.
- IF PREGNANT OR BREAST-FEEDING, consult a veterinarian before use.
- If symptoms worsen or persist for more than a week, stop use and consult a veterinarian.
- Do not use if TAMPER EVIDENT neck seal is broken or missing.

DOSAGE AND ADMINISTRATION

DIRECTIONS: Shake well before use. Mix with food or administer directly in mouth 3 - 5 times a day.

- Cats and dogs under 20 lbs: 10 drops
- Dogs 20 - 50 lbs: 15 drops
- Dogs over 50 lbs: 20 drops

In acute cases, one dose every 15 minutes up to six doses may be provided. Repeat as needed for prevention.

INACTIVE INGREDIENT

INACTIVE INGREDIENTS: Citric Acid, Vegetable Glycerin USP, Potassium Sorbate, Purified Water.

QUESTIONS

Distributed by:

PRANA PETS / Boca Raton, FL 33432

www.pranapets.com

PACKAGE LABEL

PRANA PETS

Sinu Help

Relieves symptoms related to sinus infections in cats and dogs**

Homeopathic Remedy

2 fl oz (59 mL) / Alcohol Free

Made in USA

Pharmaceutical Grade Natural Remedy